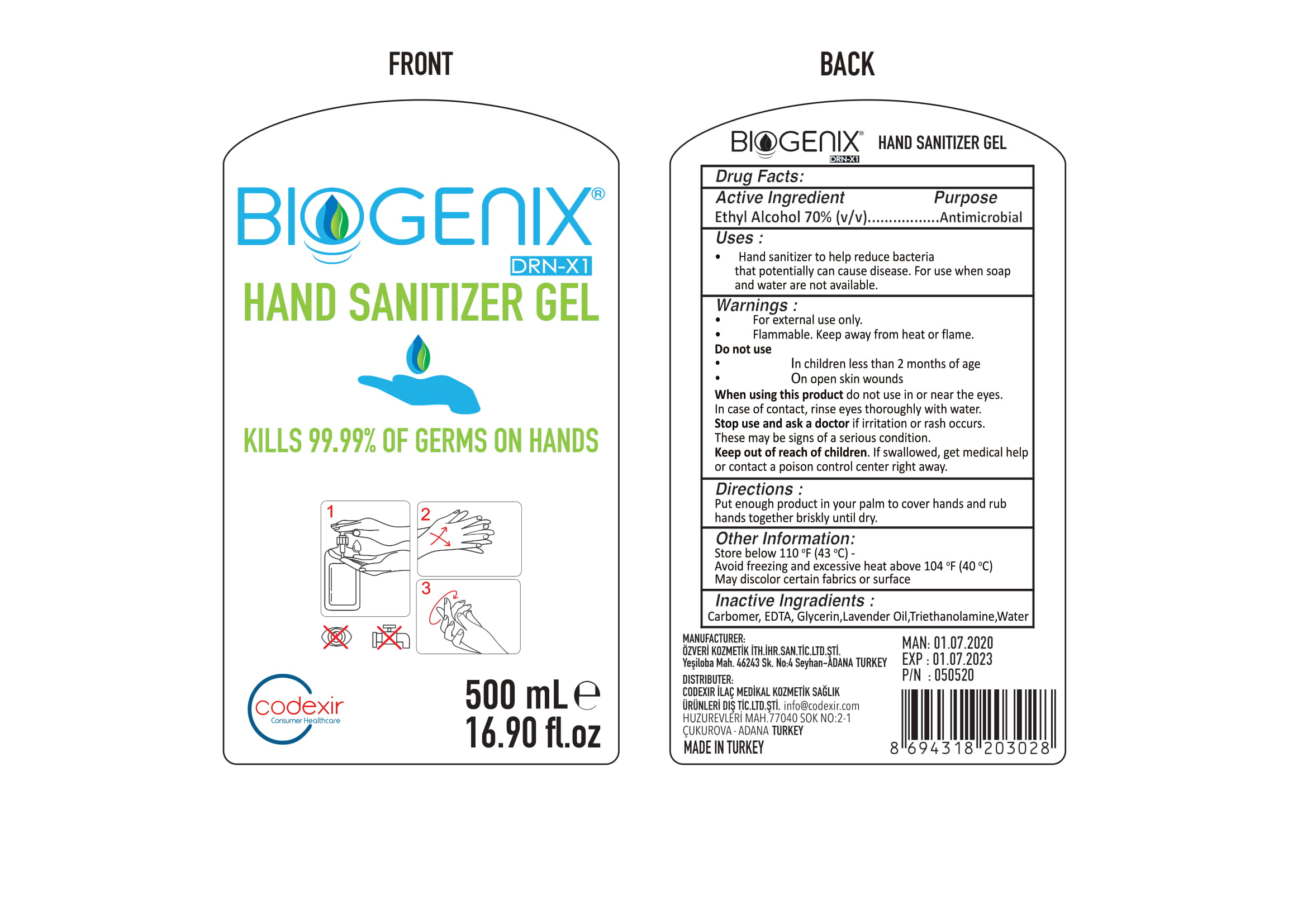 DRUG LABEL: BIOGENIX Hand Sanitizer Gel
NDC: 86943-001 | Form: GEL
Manufacturer: OZVERI KOZMETIK ITHALAT IHRACAT SAN TIC LTD STI
Category: otc | Type: HUMAN OTC DRUG LABEL
Date: 20200718

ACTIVE INGREDIENTS: ALCOHOL 70 mL/100 mL
INACTIVE INGREDIENTS: CARBOMER 940 0.5 mL/100 mL; ETIDRONATE TETRASODIUM 0.2 mL/100 mL; GLYCERIN 1.2 mL/100 mL; TROLAMINE 0.2 mL/100 mL; WATER; LAVENDER OIL 0.7 mL/100 mL

BIOGENIX HAND SANITIZER GEL

This is a hand sanitizer manufactured according to the Temporary Policy for Preparation of Certain Alcohol-Based Hand Sanitizer Products During the Public Health Emergency (CoViD-19); Guidance for Industry.

The hand sanitizer is manufactured using only the following United States Pharmacopoeia (USP) grade ingredients in the preparation of the product (percentage in final product formulation) consistent with World Health Organization (WHO) recommendations:

1. Alcohol (ethanol) (USP or Food Chemical Codex (FCC) grade) (70%, volume/volume (v/v)) in an aqueous solution denatured according to Alcohol and Tobacco Tax and Trade Bureau regulations in 27 CFR part 20.
2. Glycerol (1.2% v/v).
3. Triethanolamin (0.2% v/v).
4. EDTA (0.2% v/v).
5. Carbomer (0.5% v/v).
6. Lavander Oil (0.7% v/v).
7. water

The firm does not add other active or inactive ingredients. Different or additional ingredients may impact the quality and potency of the product.

Active Ingredient(s)

Ethyl Alcohol 70% (v/v), Antimicrobial

Purpose

Antimicrobial, Hand Sanitizer

Use

Hand Sanitizer to help reduce bacteria that potentially can cause disease. For use when soap and water are not available.

Warnings

For external use only. Flammable. Keep away from heat or flame

Do not use

- in children less than 2 months of age
- on open skin wounds

When using this product do not use in or near the eyes. In case of contact with eyes, rinse eyes thoroughly with water.
Stop use and ask a doctor if irritation or rash occurs. These may be signs of a serious condition.
Keep out of reach of children. If swallowed, get medical help or contact a Poison Control Center right away.

Stop use and ask a doctor if irritation or rash occurs. These may be signs of a serious condition.

Keep out of reach of children. If swallowed, get medical help or contact a Poison Control Center right away.

Directions

- Put enough product in your palm to cover hands and rub hands together briskly until dry.

Other information

- Store between 15-30C (59-86F)
- Avoid freezing and excessive heat above 40C (104F)

Inactive ingredients

Carbomer, EDTA, Glycerin, Lavander Oil, Triethanolamine, purified water